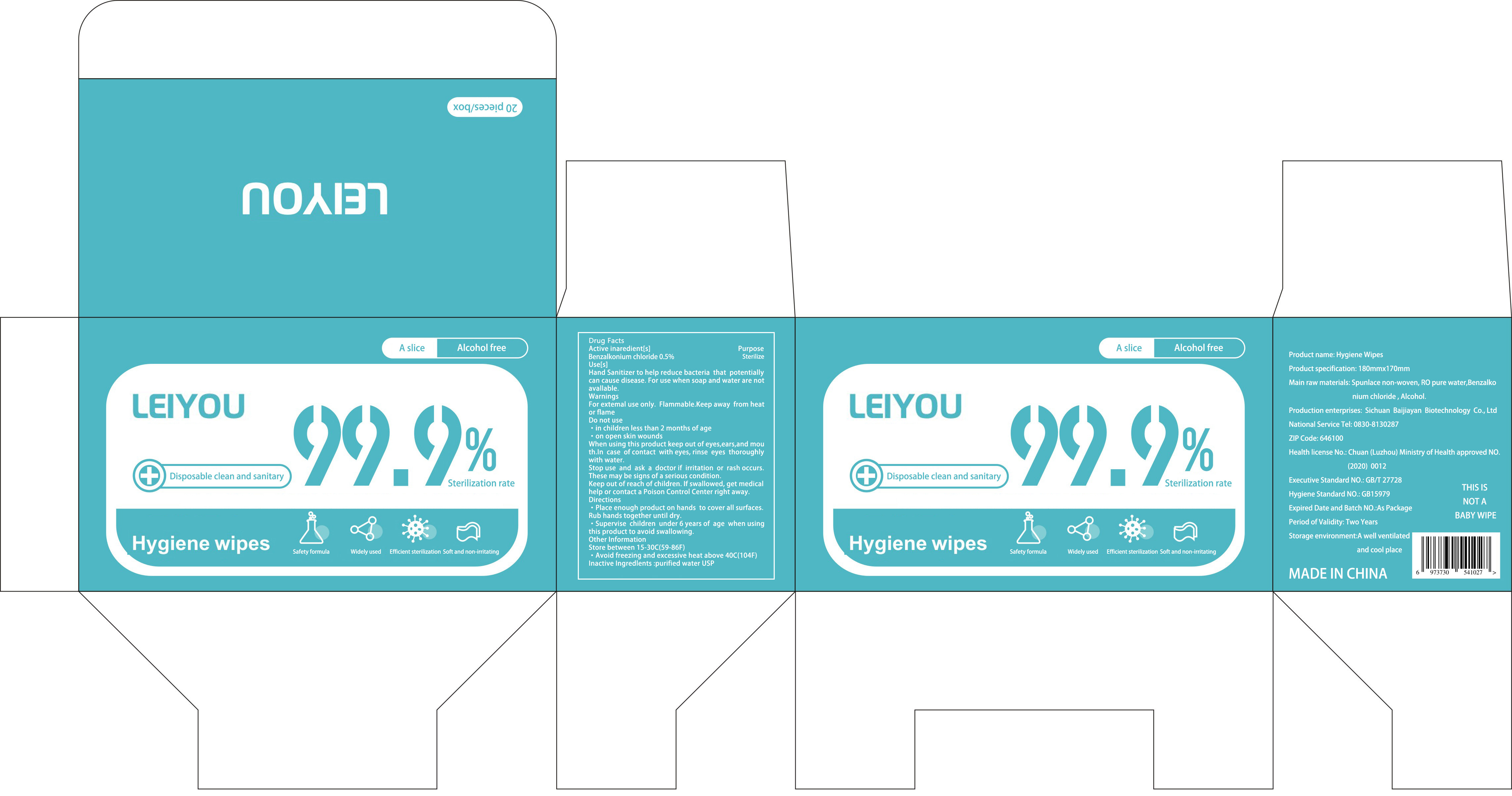 DRUG LABEL: Hygiene wipes (Non-alcohol)
NDC: 81655-001 | Form: CLOTH
Manufacturer: Sichuan Baijiayan Biotechnology Co., Ltd.
Category: otc | Type: HUMAN OTC DRUG LABEL
Date: 20210304

ACTIVE INGREDIENTS: BENZALKONIUM CHLORIDE 0.5 g/100 mL
INACTIVE INGREDIENTS: WATER

ACTIVE INGREDIENT

Benzalkonium chloride 0.5%

PURPOSE

Sterilize

Use[s]

Hand Sanitizer to help reduce bacteria that potentially can cause disease.For use when soap and water are not avallable.

WARNINGS

For extemal use only. Flammable.Keep away from heat or flame

DO NOT USE

in children less than 2 months of age

on open skin wounds

When using this product keep out of eyes,ears,and mouth.In case of contact with eyes, rinse eyes thoroughly with water.

Stop use and ask a doctor if irritation or rash occurs.These may be signs of a serious condition.

Keep out of reach of children.If swallowed,get medical help or contact a Poison Control Center right away.

Directions

Place enough product on hands to cover all surfaces.Rub hands together until dry.
Supervise children under 6 years of age when using this product to avoid swallowing.

Other Information

Store between 15-30°C(59-86°F)
Avoid freezing and excessive heat above 40°C(104°F)

INACTIVE INGREDIENT

purified water